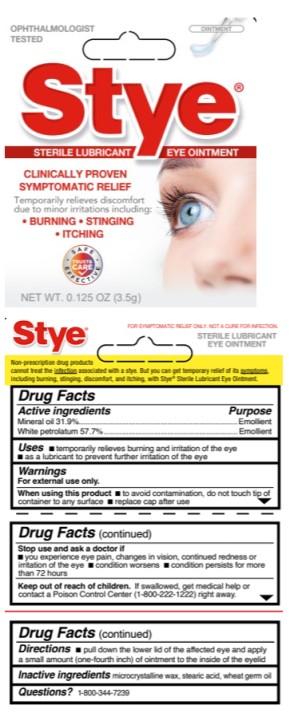 DRUG LABEL: Stye
NDC: 63736-238 | Form: GEL
Manufacturer: Insight Pharmaceuticals LLC
Category: otc | Type: HUMAN OTC DRUG LABEL
Date: 20250811

ACTIVE INGREDIENTS: MINERAL OIL 319 mg/1 g; PETROLATUM 577 mg/1 g
INACTIVE INGREDIENTS: MICROCRYSTALLINE WAX; STEARIC ACID; WHEAT GERM OIL

Stye

STYE- mineral oil and petrolatum gel
------

Stye™
Sterile Lubricant
Eye Ointment

Drug Facts

Active ingredients

Mineral oil 31.9%

Purpose

Emollient

Active ingredients

White petrolatum 57.7%

Purpose

Emollient

Uses

- temporarily relieves burning and irritation of the eye
- as a lubricant to prevent further irritation of the eye

Warnings

For external use only.

When using this product

- to avoid contamination, do not touch tip of container to any surface
- replace cap after use

Stop use and ask a doctor if

- you experience eye pain, changes in vision, continued redness or irritation of the eye
- condition worsens
- condition persists for more than 72 hours

Keep out of reach of children.

If swallowed, get medical help or contact a Poison Control Center (1-800-222-1222) right away.

Directions

- pull down the lower lid of the affected eye and apply a small amount (one-fourth inch) of ointment to the inside of the eyelid

Inactive Ingredients

microcrystalline wax, stearic acid, wheat germ oil

Questions?

1-800-344-7239

PRINCIPAL DISPLAY PANEL

Stye™
Sterile Lubricant
Eye Ointment
NET WT. 0.125 OZ (3.5g)